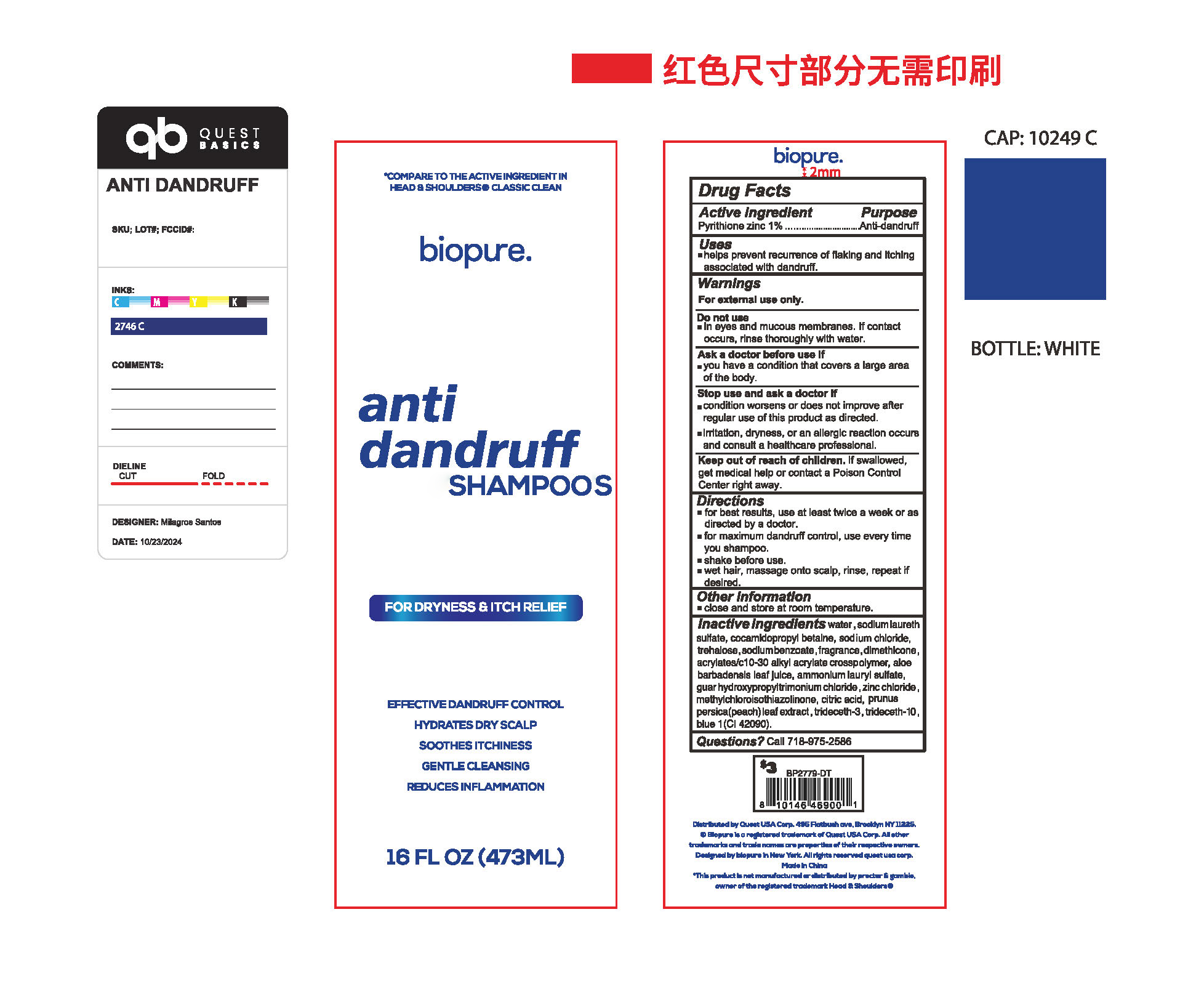 DRUG LABEL: anti dandruff SHAMPOOS
NDC: 85434-001 | Form: LIQUID
Manufacturer: Guangdong Quaker Daily Chemical Co., LTD
Category: otc | Type: HUMAN OTC DRUG LABEL
Date: 20250325

ACTIVE INGREDIENTS: PYRITHIONE ZINC 1 g/100 mL
INACTIVE INGREDIENTS: SODIUM CHLORIDE; ZINC CHLORIDE; METHYLCHLOROISOTHIAZOLINONE; TRIDECETH-10; WATER; SODIUM LAURETH SULFATE; PRUNUS PERSICA LEAF; ALOE BARBADENSIS LEAF POWDER; AMMONIUM LAURYL SULFATE; FRAGRANCE 13576; COCAMIDOPROPYL BETAINE; SODIUM BENZOATE; DIMETHICONE; CITRIC ACID; GUAR HYDROXYPROPYLTRIMONIUM CHLORIDE; ACRYLATES/C10-30 ALKYL ACRYLATE CROSSPOLYMER (60000 MPA.S); TRIDECETH-3; TREHALOSE; CI 42090

anti dandruff SHAMPOOS

ACTIVE INGREDIENT

Pyrithione zinc 1%

PURPOSE

Anti-dandruf

INDICATIONS AND USAGE

helps prevent recurence of flaking and itchlngassoclated wlth dandnrff

WARNINGS

For oxternal use only.

DO NOT USE

In eyes and mucous membranes. lf contactoccurs, rinse thoroughly with water.

WHEN USING

you have a condition that covers a large areaof the bady.

STOP USE

condition worsens or does not imprve afterregular use of this prpduct as directed.
Iritation, dryness, or an allerglc reactlon occur8and consult a healthcare professlonal.

KEEP OUT OF REACH OF CHILDREN

get medical help or contact a Poison ContolCenter right away.

DOSAGE AND ADMINISTRATION

for best results, use at least twlce a week or asdirected by a doctor.
for maxirnum dandnrff contrl, use every timeyou shampoo.
shake before use
wet hair, massage onto scalp, rinse, repeat ifdeslred.

INACTIVE INGREDIENT

water
sodium laureth sulfate
cocamidopropyl betaine
guar hydroxypropyltrimonium chloride
acrylates/c10-30 alkyl acrylate crosspolymer
zinc chloride
sodium chloride
methylchloroisothiazolinone
dimethicone
trideceth-3
trideceth-10
citric acid
prunus persica (peach) leaf extract
trehalose
aloe barbadensis leaf juice
ammonium lauryl sulfate
sodium benzoate
fragrance
blue 1 CI 42090